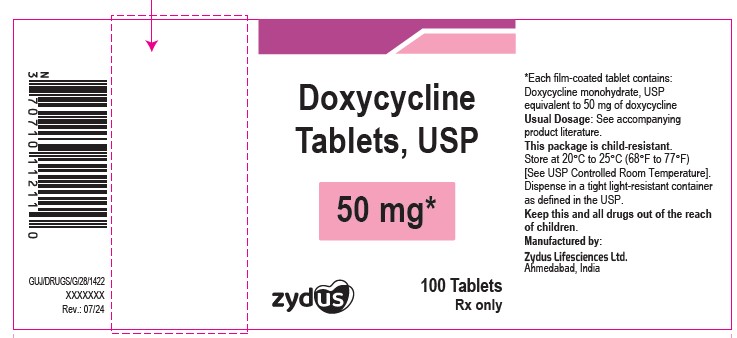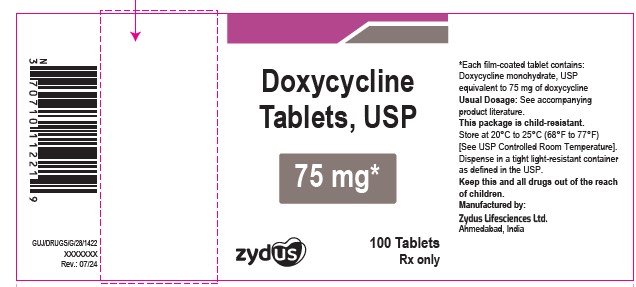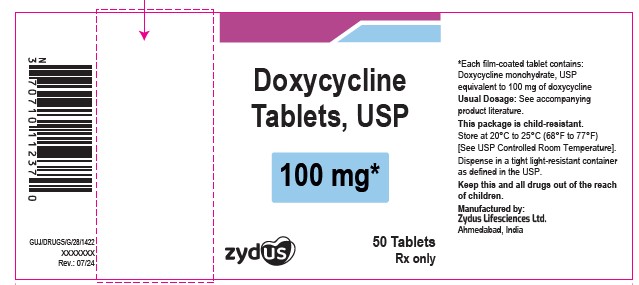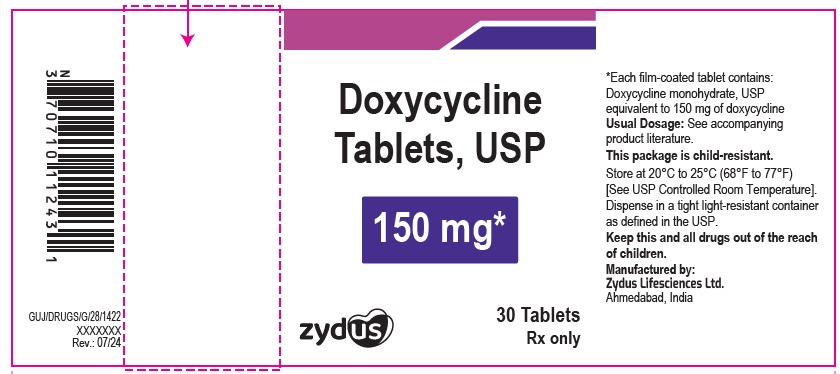 DRUG LABEL: Doxycycline
NDC: 70771-1006 | Form: TABLET, FILM COATED
Manufacturer: Zydus Lifesciences Limited
Category: prescription | Type: HUMAN PRESCRIPTION DRUG LABEL
Date: 20241128

ACTIVE INGREDIENTS: DOXYCYCLINE 50 mg/1 1
INACTIVE INGREDIENTS: CELLULOSE, MICROCRYSTALLINE; CROSPOVIDONE; D&C YELLOW NO. 10; FD&C BLUE NO. 2; FERRIC OXIDE YELLOW; HYPROMELLOSES; MAGNESIUM STEARATE; POLYETHYLENE GLYCOL, UNSPECIFIED; POLYSORBATE 80; SILICON DIOXIDE; TITANIUM DIOXIDE

Doxycycline Tablets, USP

PACKAGE LABEL.PRINCIPAL DISPLAY PANEL

NDC 70771-1006-1

Doxycycline Tablets, USP – 50 mg

Rx only

100 Tablets

NDC 70771-1007-1

Doxycycline Tablets, USP – 75 mg

Rx only

100 Tablets

NDC 70771-1008-7

Doxycycline Tablets, USP – 100 mg

Rx only

50 Tablets

NDC 70771-1009-1

Doxycycline Tablets, USP – 150 mg

Rx only

100 Tablets